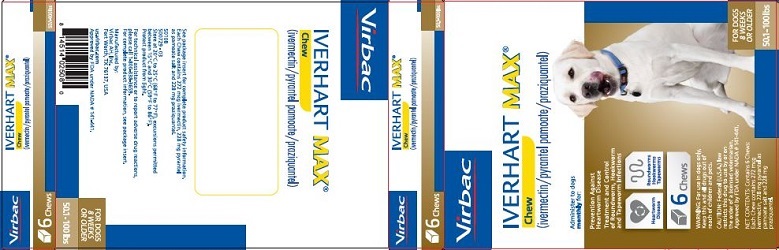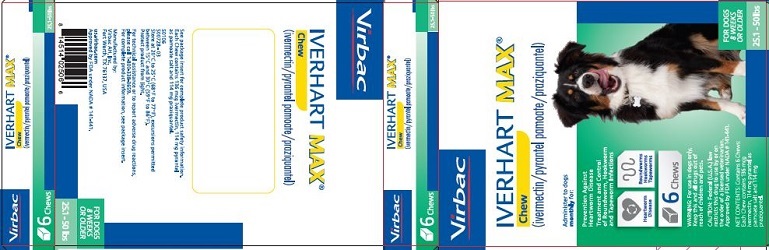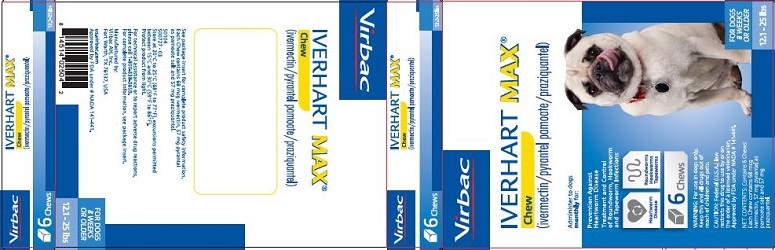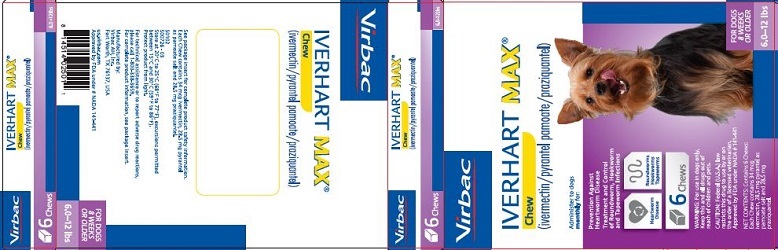 DRUG LABEL: IVERHART MAX Chew
NDC: 51311-504 | Form: TABLET, CHEWABLE
Manufacturer: Virbac AH, Inc
Category: animal | Type: PRESCRIPTION ANIMAL DRUG LABEL
Date: 20240212

ACTIVE INGREDIENTS: IVERMECTIN 34 ug/1 1; PYRANTEL PAMOATE 28.5 mg/1 1; PRAZIQUANTEL 28.5 mg/1 1

IVERHART MAX® Chew (ivermectin/pyrantel pamoate/praziquantel)

GENERAL PRECAUTIONS

For oral use in dogs only.

Caution: Federal (U.S.A.) law restricts this drug to use by or on the order of a licensed veterinarian.

Description

IVERHART MAX® Chew is a combination of three anthelmintics (ivermectin/pyrantel pamoate/praziquantel). The chews are available in four sizes in color-coded packages for oral administration to dogs according to their weight (see Dosage and Administration).

Indications

For use in dogs to prevent canine heartworm disease by eliminating the tissue stage of heartworm larvae (Dirofilaria immitis) for a month (30 days) after infection and for the treatment and control of roundworms (Toxocara canis, Toxascaris leonina), hookworms (Ancylostoma
caninum, Uncinaria stenocephala, Ancylostoma braziliense), and tapeworms (Dipylidium caninum, Taenia pisiformis).

Dosage and Administration

IVERHART MAX Chew should be administered orally at monthly intervals and the recommended minimum dose level of 6 mcg of ivermectin per kilogram (2.72 mcg/ lb), 5 mg of pyrantel (as pamoate salt) per kg (2.27 mg/lb), and 5 mg of praziquantel per kg (2.27 mg/lb) of body weight, as follows:

Dosing Schedule
Dog Weight Pounds | Chew per Month | Chew Size | Ivermectin Content | Pyrantel Pamoate Content | Praziquantel Content
6.0 to 12 | 1 | Toy | 34 mcg | 28.5 mg | 28.5 mg
12.1 to 25 | 1 | Small | 68 mcg | 57 mg | 57 mg
25.1 to 50 | 1 | Medium | 136 mcg | 114 mg | 114 mg
50.1 to 100 | 1 | Large | 272 mcg | 228 mg | 228 mg

IVERHART MAX Chew is recommended for dogs 8 weeks of age or older. For dogs over 100 lbs, use the appropriate combination of these chews. Remove only one dose at a time from the packaging. Return the remaining chew(s) to their box to protect from light. The chew can be offered to the dog by hand or added, intact, to a small amount of dog food. Care should be taken to ensure that the dog consumes the complete dose. The treated dog should be observed for a few minutes after administration to confirm that none of the dose has been lost or rejected. If it is suspected that any of the dose has been lost, redosing is recommended.

IVERHART MAX Chew should be given at monthly intervals during the period of the year when mosquitoes (vectors), potentially carrying infective heartworm larvae, are active. The initial dose must be given within a month (30 days) after the dog’s first exposure to mosquitoes. The final dose must be given within a month (30 days) after the dog’s last exposure to mosquitoes.

When replacing another heartworm preventative product in a heartworm disease prevention program, the first dose of IVERHART MAX Chew must be given within a month (30 days) after the last dose of the former medication. A heartworm test should be performed prior to and 6 months after switching heartworm preventative products.

If the interval between doses exceeds a month (30 days), the effectiveness of ivermectin can be reduced. Therefore, for optimal performance, the chew must be given once a month on or about the same day of the month. If treatment is delayed, whether by a few days or many, immediate treatment with IVERHART MAX Chew and resumption of the recommended dosing regimen will minimize the opportunity for the development of adult heartworms.

Warnings

For use in dogs only. Keep this and all drugs out of reach of children and pets. In safety studies
with ivermectin/pyrantel pamoate/praziquantel tablets, testicular hypoplasia was observed in some
dogs receiving 3 and 5 times the maximum recommended dose monthly for 6 months (see Animal
Safety).

In case of ingestion by humans, clients should be advised to contact a physician immediately.
Physicians may contact a Poison Control Center for advice concerning cases of ingestion by humans.

Precautions

Use with caution in sick, debilitated, or underweight animals and dogs weighing less than 10 lbs (see Animal Safety). The safe use of this drug has not been evaluated in pregnant or lactating bitches.

All dogs should be tested for existing heartworm infection before and 6 months after starting treatment with IVERHART MAX Chew, which is not effective against adult Dirofiliaria immitis. Infected dogs should be treated to remove adult heartworms and microfilariae before initiating a heartworm prevention program.

While some microfilariae may be killed by the ivermectin in IVERHART MAX Chew at the recommended dose level, IVERHART MAX Chew is not effective for microfilariae clearance. A mild hypersensitivity-type reaction, presumably due to dead or dying microfilariae and particularly involving a transient diarrhea, has been observed in clinical trials with ivermectin alone after treatment of some dogs that have circulating microfilariae.

Adverse Reactions

In a field study with IVERHART MAX Chew, self-limiting adverse reactions, including vomiting, diarrhea, lethargy, difficulty swallowing, excessive salivation, increased water consumption, and coughing were reported. Self-limiting adverse reactions, including lethargy, limpness, salivation, shaking, diarrhea, decreased appetite, licking lips, and belching were reported between 20 minutes and 72 hours following treatment in a field study with ivermectin/pyrantel pamoate/praziquantel tablets.

In field studies with ivermectin/pyrantel/praziquantel pamoate tablets, vomiting or diarrhea within 24 hours of dosing was rarely observed (1.1% of administered doses). The following adverse reactions have been reported in dogs following the use of ivermectin products: depression/lethargy, vomiting,anorexia, diarrhea, mydriasis, ataxia, staggering, convulsions, and hypersalivation.

To report suspected adverse events, for technical assistance or to obtain a copy of the Safety Data Sheet (SDS), contact Virbac AH, Inc. at 1-800-338-3659 or us.virbac.com. For additional information about adverse drug experience reporting for animal drugs, contact the FDA at 1-888-FDA-VETS or www.fda.gov/reportanimalae.

CLINICAL STUDIES

Effectiveness: Prevention of the tissue larval stage of heartworm (Dirofilaria immitis) and the elimination of the adult stage of hookworm (Ancylostoma caninum, Uncinaria stenocephala, Anyclostoma braziliense), roundworm (Toxocara canis, Toxascaris leonina), and tapeworm (Dipylidium
caninum, Taenia pisiformis) infections in dogs was demonstrated in well-controlled laboratory studies.

Palatability: In a field study of 132 dogs, IVERHART MAX Chew was offered once monthly for 3 months. The dogs voluntarily consumed 86.3% of the doses from the owner’s hand or from a bowl within 5 minutes, 13.0% accepted the dose when it was offered in food or administered by placing in the back of the dog’s tongue (pilling), and 0.7% of the doses were unable to be administered.

Animal Safety

Studies with ivermectin indicate that certain dogs of the Collie breed are more sensitive to the effects of ivermectin administered at elevated dose levels (more than 16 times the target dose level of 6 mcg/kg) than dogs of other breeds. At elevated doses, sensitive dogs showed more adverse
reactions which included mydriasis, depression, ataxia, tremors, drooling, paresis, recumbency, excitability, stupor, coma and death. No signs of toxicity were seen at 10 times the recommended dose (27.2 mcg/lb) in sensitive Collies. Data from these studies support the safety of ivermectin products in dogs, including Collies, when used at the label recommended dose.

Because ivermectin and praziquantel are approximately 30% more bioavailable in the IVERHART MAX Chew than in the ivermectin/pyrantel pamoate/praziquantel tablets used in the following target animal safety studies, the margin of safety is narrower than reported in these studies. The potential for adverse reactions may be greater in individual dogs administered IVERHART MAX Chew than ivermectin/pyrantel pamoate/praziquantel tablets.

In a target animal safety study using ivermectin/pyrantel pamoate/praziquantel tablets, doses were administered to 8 week old Beagle puppies at one, three, and five times the maximum recommended dose of 12.5 mcg/kg ivermectin, 10.47 mg/kg pyrantel and 10.47 mg/kg praziquantel. The dogs were treated every 30 days for 6 months. Vomiting within 6 hours of dosing and soft or watery feces within 24 hours of dosing were observed. Other observations during the study were: ano-genital swelling, lethargy, head movements, shallow, audible or difficult breathing, and salivation. One dog in the 5X group had tremors and decreased activity. All of these signs were transient. No treatment was required. Histopathology showed testicular hypoplasia in the 3X and 5X groups (see Warnings).

In a laboratory safety study using ivermectin/pyrantel pamoate/praziquantel tablets, 12-week-old Beagle puppies receiving 3 and 5 times the recommended dose once weekly for 13 weeks demonstrated a dose-related decrease in testicular maturation compared to controls. In this study, all treated puppies had significantly higher cholesterol levels compared to untreated controls.

In a reproductive safety study, adult males were treated at 37.5 mcg/kg ivermectin, 31.4 mg/kg pyrantel and 31.4 mg/kg praziquantel every 14 days during two full spermatogenic cycles (112 days). The quality of semen and reproductive health were not affected by treatment. Treatment related vomiting and soft feces were reported during this study.

In a study of the effectiveness of ivermectin/pyrantel pamoate/praziquantel tablets for the treatment of Toxocara canis, one 8.1 lb, 72-day-old puppy died 6 days after administration of the label dose. This puppy and many other puppies in the study had high worm burdens and were reported to have diarrhea, sometimes bloody, frequently before and after treatment. Dehydration and signs of anemia (pale mucous membranes) were the only abnormal gross necropsy finding observed. No definitive cause was determined. In a 90-day field study using ivermectin/pyrantel pamoate/praziquantel tablets, the most serious adverse reactions (lethargy, limpness, and salivation) were seen in dogs weighing less than 10 lbs (see Precautions).

Storage Information

Store at 20°C to 25°C (68°F to 77°F), excursions permitted between 15°C and 30°C (59°F to 86°F). Protect product from light.

How Supplied

IVERHART MAX Chew is available in four dosage strengths (see Dosage and Administration) for dogs of different weights. Each strength comes in a package of 6 chews.

Approved by FDA under NADA # 141-441

Manufactured by:
Virbac AH, Inc.
Fort Worth, TX 76137 USA
Phone: 1-800-338-3659

© 2020 Virbac Corporation. IVERHART MAX is a registered trademark of Virbac Corporation. 302143-04
10/2020